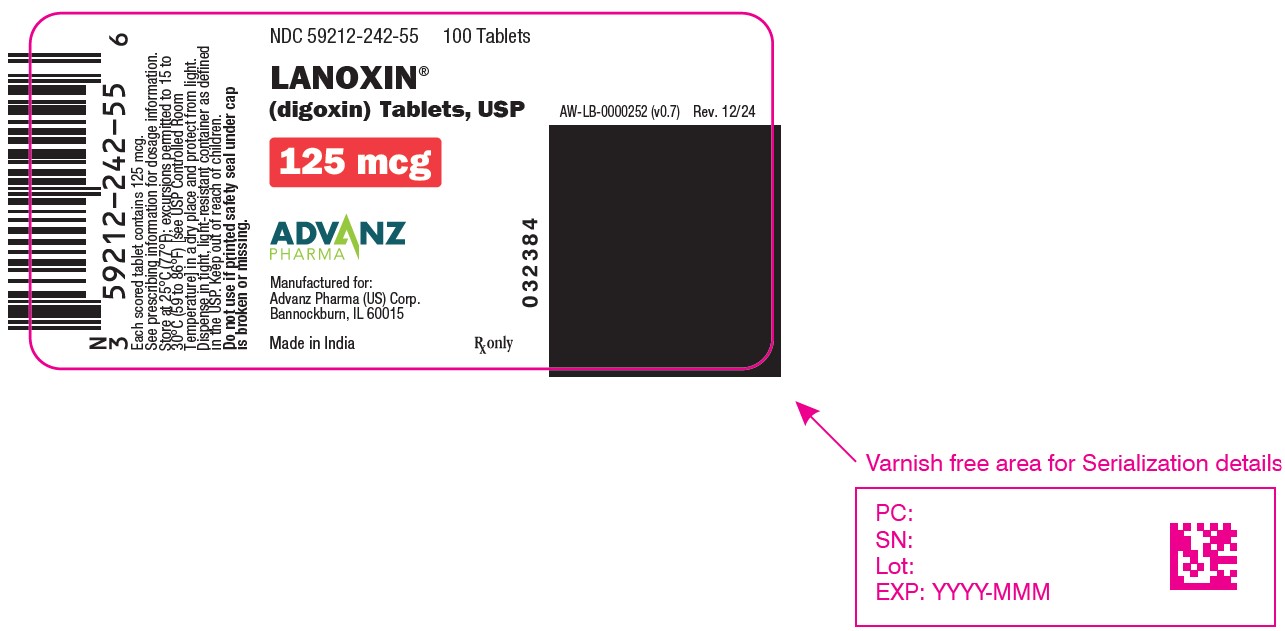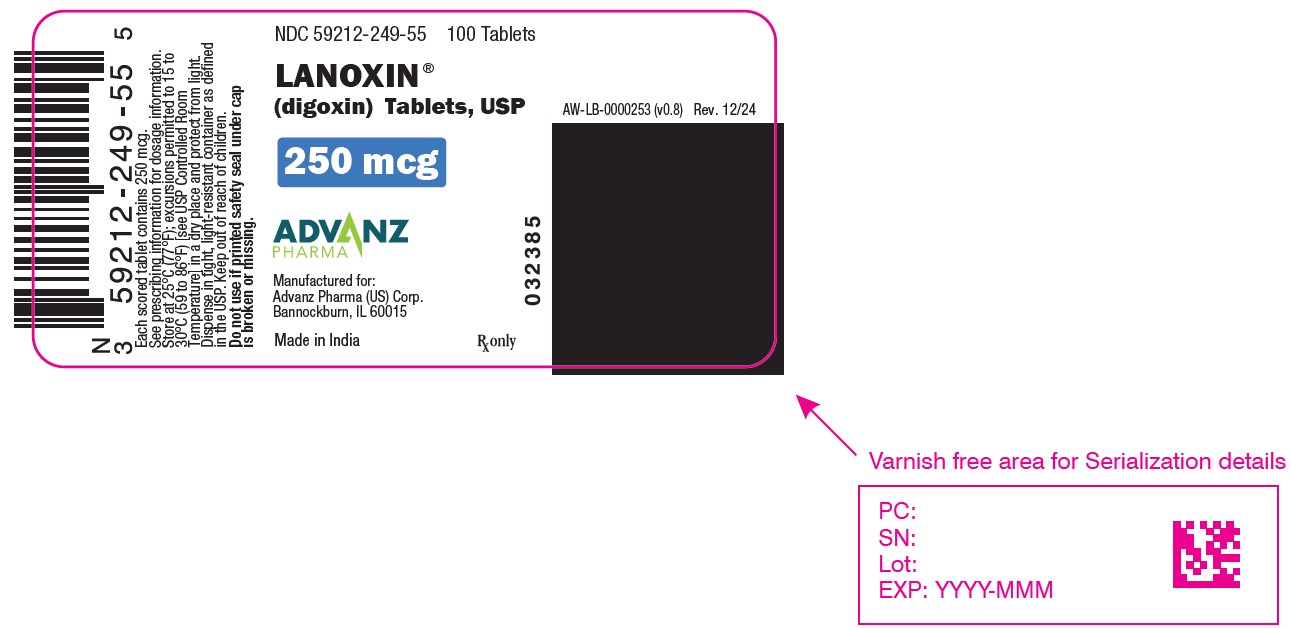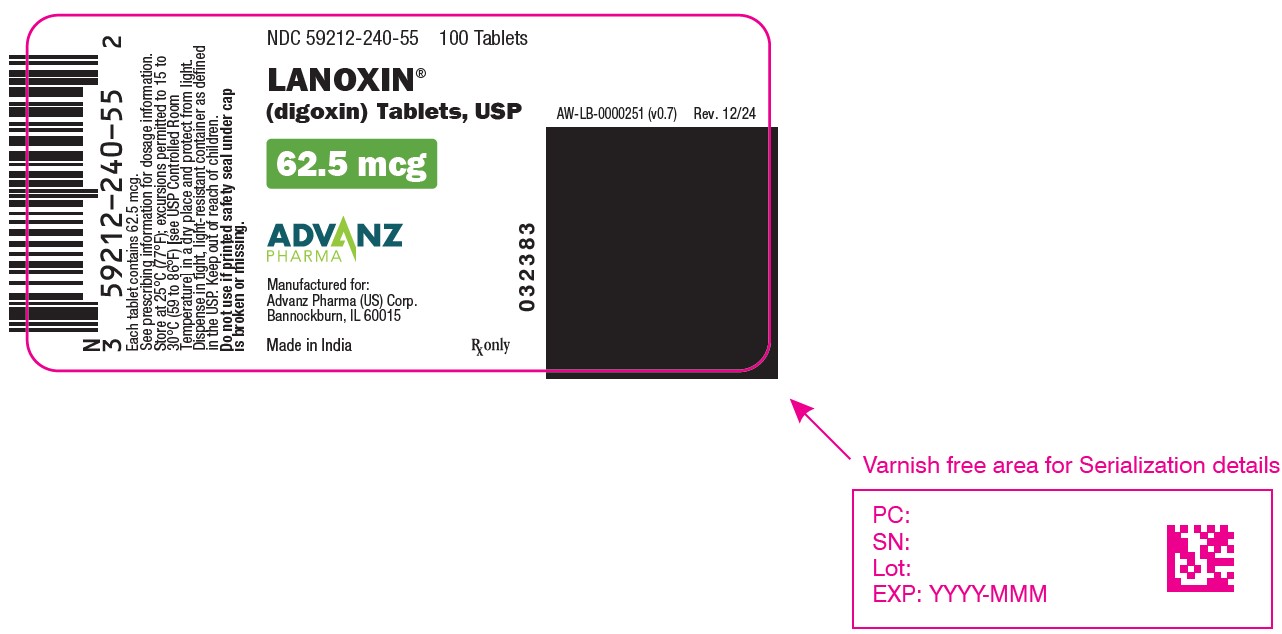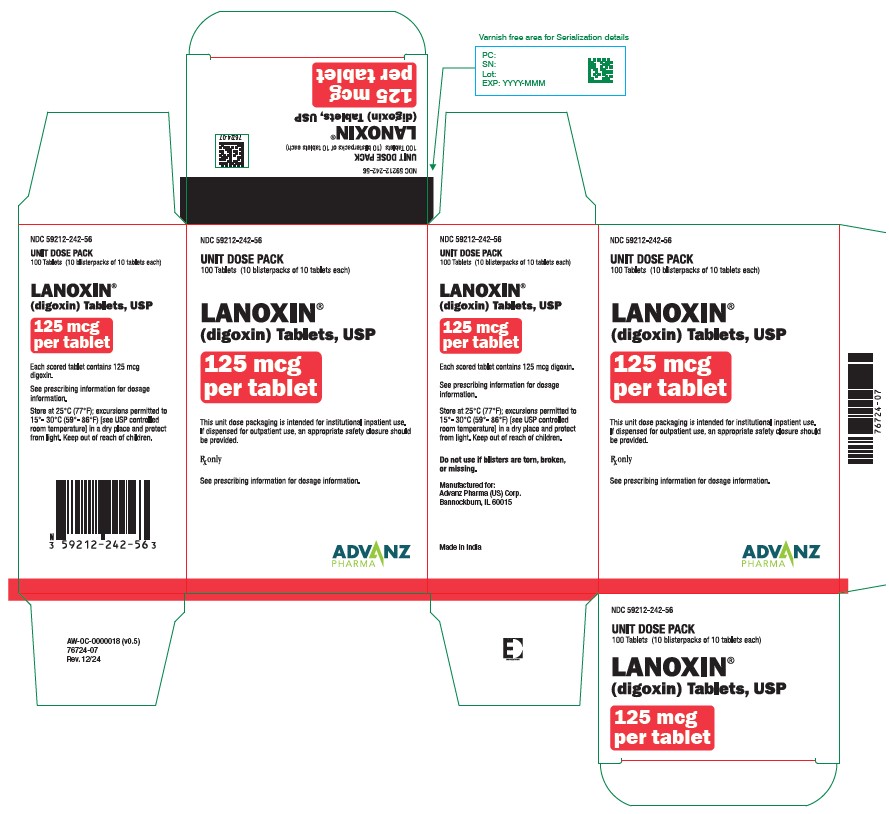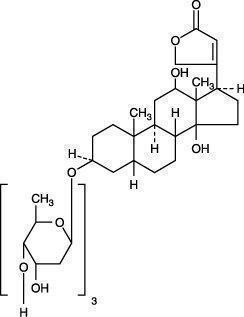 DRUG LABEL: LANOXIN
NDC: 59212-242 | Form: TABLET
Manufacturer: Advanz Pharma (US) Corp.
Category: prescription | Type: Human Prescription Drug Label
Date: 20241205

ACTIVE INGREDIENTS: DIGOXIN 0.125 mg/1 1
INACTIVE INGREDIENTS: STARCH, POTATO; STARCH, CORN; LACTOSE MONOHYDRATE; MAGNESIUM STEARATE; D&C YELLOW NO. 10; FD&C YELLOW NO. 6

HIGHLIGHTS OF PRESCRIBING INFORMATION

These highlights do not include all the information needed to use LANOXIN safely and effectively. See full prescribing information for LANOXIN.
LANOXIN® (digoxin) tablets, for oral use
Initial U.S. Approval: 1954

1 INDICATIONS AND USAGE

LANOXIN is a cardiac glycoside indicated for:

- Treatment of mild to moderate heart failure in adults. (1.1)
- Increasing myocardial contractility in pediatric patients with heart failure. (1.2)
- Control of resting ventricular rate in patients with chronic atrial fibrillation in adults. (1.3)

2 DOSAGE AND ADMINISTRATION

LANOXIN dose is based on patient-specific factors (age, lean body weight, renal function, etc.). See full prescribing information. Monitor for toxicity and therapeutic effect. (2)

3 DOSAGE FORMS AND STRENGTHS

Unscored Tablets: 62.5 mcg. Scored Tablets 125 and 250 mcg. (3)

4 CONTRAINDICATIONS

- Ventricular fibrillation. (4)
- Known hypersensitivity to digoxin or other forms of digitalis. (4)

5 WARNINGS AND PRECAUTIONS

- Risk of rapid ventricular response leading to ventricular fibrillation in patients with AV accessory pathway. (5.1)
- Risk of advanced or complete heart block in patients with sinus node disease and AV block. (5.2)
- Digoxin toxicity: Indicated by nausea, vomiting, visual disturbances, and cardiac arrhythmias. Advanced age, low body weight, impaired renal function and electrolyte abnormalities predispose to toxicity. (5.3)
- Risk of ventricular arrhythmias during electrical cardioversion. (5.4)
- Not recommended in patients with acute myocardial infarction. (5.5)
- Avoid LANOXIN in patients with myocarditis. (5.6)

6 ADVERSE REACTIONS

The overall incidence of adverse reactions with digoxin has been reported as 5-20%, with 15-20% of adverse events considered serious. Cardiac toxicity accounts for about one-half, gastrointestinal disturbances for about one-fourth, and CNS and other toxicity for about one-fourth of these adverse events. (6.1)

To report SUSPECTED ADVERSE REACTIONS, contact Advanz Pharma (US) Corp. at 1-877-370-1142 or FDA at 1-800-FDA-1088 or www.fda.gov/medwatch.

7 DRUG INTERACTIONS

- PGP Inducers/Inhibitors: Drugs that induce or inhibit PGP have the potential to alter digoxin pharmacokinetics. (7.1)
- The potential for drug-drug interactions must be considered prior to and during drug therapy. See full prescribing information. (7.2, 7.3, 12.3)

8 USE IN SPECIFIC POPULATIONS

- Pregnant patients: It is unknown whether use during pregnancy can cause fetal harm. (8.1)
- Pediatric patients: Newborn infants display variability in tolerance to LANOXIN. (8.4)
- Geriatric patients: Consider renal function in dosage selection, and carefully monitor for side effects. (8.5)
- Renal impairment: LANOXIN is excreted by the kidneys. Consider renal function during dosage selection. (8.6)

FULL PRESCRIBING INFORMATION

1 INDICATIONS AND USAGE

1.1 Heart Failure in Adults

LANOXIN is indicated for the treatment of mild to moderate heart failure in adults. LANOXIN increases left ventricular ejection fraction and improves heart failure symptoms as evidenced by improved exercise capacity and decreased heart failure-related hospitalizations and emergency care, while having no effect on mortality. Where possible, LANOXIN should be used in combination with a diuretic and an angiotensin-converting enzyme (ACE) inhibitor.

1.2 Heart Failure in Pediatric Patients

LANOXIN increases myocardial contractility in pediatric patients with heart failure.

1.3 Atrial Fibrillation in Adults

LANOXIN is indicated for the control of ventricular response rate in adult patients with chronic atrial fibrillation.

2 DOSAGE AND ADMINISTRATION

2.1 Important Dosing and Administration Information

In selecting a LANOXIN dosing regimen, it is important to consider factors that affect digoxin blood levels (e.g., body weight, age, renal function, concomitant drugs) since toxic levels of digoxin are only slightly higher than therapeutic levels. Dosing can be either initiated with a loading dose followed by maintenance dosing if rapid titration is desired or initiated with maintenance dosing without a loading dose.

Consider interruption or reduction in LANOXIN dose prior to electrical cardioversion [see Warnings and Precautions (5.4)].

Use digoxin solution to obtain the appropriate dose in infants, young pediatric patients, or patients with very low body weight.

2.2 Loading Dosing Regimen in Adults and Pediatric Patients

For adults and pediatric patients if a loading dosage is to be given, administer half the total loading dose initially, then ¼ the loading dose every 6-8 hours twice, with careful assessment of clinical response and toxicity before each dose. The recommended loading dose is displayed in Table 1.

Table 1. Recommended LANOXIN Oral Loading Dose
Age | Total Oral Loading Dose (mcg/kg) Administer half the total loading dose initially, then ¼ the loading dose every 6 to 8 hours twice
5 to 10 years | 20-45
Adults and pediatric patients over 10 years | 10-15

mcg = microgram

2.3 Maintenance Dosing in Adults and Pediatric Patients Over 10 Years Old

The maintenance dose is based on lean body weight, renal function, age, and concomitant products [see Clinical Pharmacology (12.3)].

The recommended starting maintenance dose in adults and pediatric patients over 10 years old with normal renal function is given in Table 2. Doses may be increased every 2 weeks according to clinical response, serum drug levels, and toxicity.

Table 2. Recommended Starting LANOXIN Maintenance Dosage in Adults and Pediatric Patients Over 10 Years Old
Age | Total Oral Maintenance Dose, mcg/kg/day (given once daily)
Adults and pediatric patients over 10 years | 3.4-5.1

mcg = microgram

Table 3 provides the recommended (once daily) maintenance dose for adults and pediatric patients over 10 years old (to be given once daily) according to lean body weight and renal function. The doses are based on studies in adult patients with heart failure. Alternatively, the maintenance dose may be estimated by the following formula (peak body stores lost each day through elimination):

Total Maintenance Dose = Loading Dose (i.e., Peak Body Stores) x % Daily Loss/100
(% Daily Loss = 14 + Creatinine clearance/5)

Reduce the dose of LANOXIN in patients whose lean weight is an abnormally small fraction of their total body mass because of obesity or edema.

Table 3. Recommended Maintenance Dose (in micrograms given once daily) of LANOXIN in Pediatric Patients Over 10 Years Old and Adults by Lean Body Weight and by Renal Functiona
Corrected Creatinine Clearanceb | Lean Body Weightd |  |  |  |  |  |  |  | Number of Days Before Steady State Achievedc
Corrected Creatinine Clearanceb | kg | 40 | 50 | 60 | 70 | 80 | 90 | 100 | Number of Days Before Steady State Achievedc
10 mL/min |  | 62.5* | 125 | 125 | 187.5 | 187.5 | 187.5 | 250 | 19
20 mL/min |  | 125 | 125 | 125 | 187.5 | 187.5 | 250 | 250 | 16
30 mL/min |  | 125 | 125 | 187.5 | 187.5 | 250 | 250 | 312.5 | 14
40 mL/min |  | 125 | 187.5 | 187.5 | 250 | 250 | 312.5 | 312.5 | 13
50 mL/min |  | 125 | 187.5 | 187.5 | 250 | 250 | 312.5 | 312.5 | 12
60 mL/min |  | 125 | 187.5 | 250 | 250 | 312.5 | 312.5 | 375 | 11
70 mL/min |  | 187.5 | 187.5 | 250 | 250 | 312.5 | 375 | 375 | 10
80 mL/min |  | 187.5 | 187.5 | 250 | 312.5 | 312.5 | 375 | 437.5 | 9
90 mL/min |  | 187.5 | 250 | 250 | 312.5 | 375 | 437.5 | 437.5 | 8
100 mL/min |  | 187.5 | 250 | 312.5 | 312.5 | 375 | 437.5 | 500 | 7

a Doses are rounded to the nearest dose possible using whole LANOXIN tablets. Recommended doses approximately 30 percent lower than the calculated dose are designated with an *. Monitor digoxin levels in patients receiving these initial doses and increase dose if needed.
b For adults, creatinine clearance was corrected to 70-kg body weight or 1.73 m^2 body surface area. If only serum creatinine concentrations (Scr) are available, a corrected Ccr may be estimated in men as (140 – Age)/Scr. For women, this result should be multiplied by 0.85.
For pediatric patients, the modified Schwartz equation may be used. The formula is based on height in cm and Scr in mg/dL where k is a constant. Ccr is corrected to 1.73 m^2 body surface area. During the first year of life, the value of k is 0.33 for pre-term babies and 0.45 for term infants. The k is 0.55 for pediatric patients and adolescent girls and 0.7 for adolescent boys.
GFR (mL/min/1.73 m^2) = (k x Height)/Scr
c If no loading dose administered.
d The doses listed assume average body composition.

2.4 Maintenance Dosing in Pediatric Patients Less Than 10 Years Old

The starting maintenance dose for heart failure in pediatric patients less than 10 years old is based on lean body weight, renal function, age, and concomitant products [see Clinical Pharmacology (12.3)]. The recommended starting maintenance dose for pediatric patients between 5 years and 10 years old is given in Table 4. These recommendations assume the presence of normal renal function.

Table 4. Recommended Starting LANOXIN Oral Maintenance Dosage in Pediatric Patients between 5 and 10 Years Old
Age | Oral Maintenance Dose, mcg/kg/dose
5 years to 10 years | 3.2-6.4 Twice daily

Table 5 provides average daily maintenance dose requirements for pediatric patients between 5 and 10 years old (to be given twice daily) with heart failure based on age, lean body weight, and renal function.

Table 5. Recommended Maintenance Dose (in micrograms given TWICE daily) of LANOXIN in Pediatric Patients between 5 and 10 Years of Agea Based upon Lean Body Weight and Renal Functiona,b
Corrected Creatinine Clearancec | Lean Body Weight |  |  |  |  |  | Number of Days Before Steady State Achievedd
Corrected Creatinine Clearancec | kg | 20 | 30 | 40 | 50 | 60 | Number of Days Before Steady State Achievedd
10 mL/min |  | - | 62.5 | 62.5* | 125 | 125 | 19
20 mL/min |  | 62.5 | 62.5 | 125 | 125 | 125 | 16
30 mL/min |  | 62.5 | 62.5* | 125 | 125 | 187.5 | 14
40 mL/min |  | 62.5 | 62.5* | 125 | 187.5 | 187.5 | 13
50 mL/min |  | 62.5 | 125 | 125 | 187.5 | 187.5 | 12
60 mL/min |  | 62.5 | 125 | 125 | 187.5 | 250 | 11
70 mL/min |  | 62.5 | 125 | 187.5 | 187.5 | 250 | 10
80 mL/min |  | 62.5* | 125 | 187.5 | 187.5 | 250 | 9
90 mL/min |  | 62.5* | 125 | 187.5 | 250 | 250 | 8
100 mL/min |  | 62.5* | 125 | 187.5 | 250 | 312.5 | 7

a Recommended are doses to be given twice daily.
b The doses are rounded to the nearest dose possible using whole LANOXIN tablets. Recommended doses approximately 30 percent lower than the calculated dose are designated with an *. Monitor digoxin levels in patients receiving these initial doses and increase dose if needed.
c The modified Schwartz equation may be used to estimate creatinine clearance. See footnote b under Table 3.
d If no loading dose administered.

2.5 Monitoring to Assess Safety, Efficacy, and Therapeutic Blood Levels

Monitor for signs and symptoms of digoxin toxicity and clinical response. Adjust dose based on toxicity, efficacy, and blood levels.

Serum digoxin levels less than 0.5 ng/mL have been associated with diminished efficacy, while levels above 2 ng/mL have been associated with increased toxicity without increased benefit.

Interpret the serum digoxin concentration in the overall clinical context, and do not use an isolated measurement of serum digoxin concentration as the basis for increasing or decreasing the LANOXIN dose. Serum digoxin concentrations may be falsely elevated by endogenous digoxin-like substances [see Drug Interactions (7.4)]. If the assay is sensitive to these substances, consider obtaining a baseline digoxin level before starting LANOXIN and correct post-treatment values by the reported baseline level.

Obtain serum digoxin concentrations just before the next scheduled LANOXIN dose or at least 6 hours after the last dose. The digoxin concentration is likely to be 10-25% lower when sampled right before the next dose (24 hours after dosing) compared to sampling 8 hours after dosing (using once-daily dosing). However, there will be only minor differences in digoxin concentrations using twice daily dosing whether sampling is done at 8 or 12 hours after a dose.

2.6 Switching from Intravenous Digoxin to Oral Digoxin

When switching from intravenous to oral digoxin formulations, make allowances for differences in bioavailability when calculating maintenance dosages (see Table 6).

Table 6. Comparison of the Systemic Availability and Equivalent Doses of Oral and Intravenous LANOXIN
 | Absolute Bioavailability | Equivalent Doses (mcg)
LANOXIN Tablets | 60-80% | 62.5 | 125 | 250 | 500
LANOXIN Intravenous Injection | 100% | 50 | 100 | 200 | 400

3 DOSAGE FORMS AND STRENGTHS

Unscored Tablets: 62.5 mcg are peach, round with "U3A" imprinted on one side.
Scored Tablets: 125 mcg are yellow, round, scored tablets with "Y3B" imprinted on one side.
Scored Tablets: 250 mcg are white, round, scored tablets with "X3A" imprinted on one side.

4 CONTRAINDICATIONS

LANOXIN is contraindicated in patients with:

- Ventricular fibrillation [see Warnings and Precautions (5.1)]
- Known hypersensitivity to digoxin (reactions seen include unexplained rash, swelling of the mouth, lips or throat or a difficulty in breathing). A hypersensitivity reaction to other digitalis preparations usually constitutes a contraindication to digoxin.

5 WARNINGS AND PRECAUTIONS

5.1 Ventricular Fibrillation in Patients With Accessory AV Pathway (Wolff-Parkinson-White Syndrome)

Patients with Wolff-Parkinson-White syndrome who develop atrial fibrillation are at high risk of ventricular fibrillation. Treatment of these patients with digoxin leads to greater slowing of conduction in the atrioventricular node than in accessory pathways, and the risks of rapid ventricular response leading to ventricular fibrillation are thereby increased.

5.2 Sinus Bradycardia and Sino-atrial Block

LANOXIN may cause severe sinus bradycardia or sinoatrial block particularly in patients with pre-existing sinus node disease and may cause advanced or complete heart block in patients with pre-existing incomplete AV block. Consider insertion of a pacemaker before treatment with digoxin.

5.3 Digoxin Toxicity

Signs and symptoms of digoxin toxicity include anorexia, nausea, vomiting, visual changes and cardiac arrhythmias [first-degree, second-degree (Wenckebach), or third-degree heart block (including asystole); atrial tachycardia with block; AV dissociation; accelerated junctional (nodal) rhythm; unifocal or multiform ventricular premature contractions (especially bigeminy or trigeminy); ventricular tachycardia; and ventricular fibrillation]. Toxicity is usually associated with digoxin levels greater than 2 ng/ml although symptoms may also occur at lower levels. Low body weight, advanced age or impaired renal function, hypokalemia, hypercalcemia, or hypomagnesemia may predispose to digoxin toxicity. Obtain serum digoxin levels in patients with signs or symptoms of digoxin therapy and interrupt or adjust dose if necessary [see Adverse Reactions (6) and Overdosage (10)]. Assess serum electrolytes and renal function periodically.

The earliest and most frequent manifestation of digoxin toxicity in infants and children is the appearance of cardiac arrhythmias, including sinus bradycardia. In children, the use of digoxin may produce any arrhythmia. The most common are conduction disturbances or supraventricular tachyarrhythmias, such as atrial tachycardia (with or without block) and junctional (nodal) tachycardia. Ventricular arrhythmias are less common. Sinus bradycardia may be a sign of impending digoxin intoxication, especially in infants, even in the absence of first-degree heart block. Any arrhythmias or alteration in cardiac conduction that develops in a child taking digoxin should initially be assumed to be a consequence of digoxin intoxication.

Given that adult patients with heart failure have some symptoms in common with digoxin toxicity, it may be difficult to distinguish digoxin toxicity from heart failure. Misidentification of their etiology might lead the clinician to continue or increase LANOXIN dosing, when dosing should actually be suspended. When the etiology of these signs and symptoms is not clear, measure serum digoxin levels.

5.4 Risk of Ventricular Arrhythmias During Electrical Cardioversion

It may be desirable to reduce the dose of or discontinue LANOXIN for 1 to 2 days prior to electrical cardioversion of atrial fibrillation to avoid the induction of ventricular arrhythmias, but physicians must consider the consequences of increasing the ventricular response if digoxin is decreased or withdrawn. If digitalis toxicity is suspected, elective cardioversion should be delayed. If it is not prudent to delay cardioversion, the lowest possible energy level should be selected to avoid provoking ventricular arrhythmias.

5.5 Risk of Ischemia in Patients With Acute Myocardial Infarction

LANOXIN is not recommended in patients with acute myocardial infarction because digoxin may increase myocardial oxygen demand and lead to ischemia.

5.6 Vasoconstriction In Patients With Myocarditis

LANOXIN can precipitate vasoconstriction and may promote production of pro-inflammatory cytokines; therefore, avoid use in patients with myocarditis.

5.7 Decreased Cardiac Output in Patients With Preserved Left Ventricular Systolic Function

Patients with heart failure associated with preserved left ventricular ejection fraction may experience decreased cardiac output with use of LANOXIN. Such disorders include restrictive cardiomyopathy, constrictive pericarditis, amyloid heart disease, and acute cor pulmonale. Patients with idiopathic hypertrophic subaortic stenosis may have worsening of the outflow obstruction due to the inotropic effects of digoxin. Patients with amyloid heart disease may be more susceptible to digoxin toxicity at therapeutic levels because of an increased binding of digoxin to extracellular amyloid fibrils.

LANOXIN should generally be avoided in these patients, although it has been used for ventricular rate control in the subgroup of patients with atrial fibrillation.

5.8 Reduced Efficacy In Patients With Hypocalcemia

Hypocalcemia can nullify the effects of digoxin in humans; thus, digoxin may be ineffective until serum calcium is restored to normal. These interactions are related to the fact that digoxin affects contractility and excitability of the heart in a manner similar to that of calcium.

5.9 Altered Response in Thyroid Disorders and Hypermetabolic States

Hypothyroidism may reduce the requirements for digoxin.

Heart failure and/or atrial arrhythmias resulting from hypermetabolic or hyperdynamic states (e.g., hyperthyroidism, hypoxia, or arteriovenous shunt) are best treated by addressing the underlying condition. Atrial arrhythmias associated with hypermetabolic states are particularly resistant to digoxin treatment. Patients with beri beri heart disease may fail to respond adequately to digoxin if the underlying thiamine deficiency is not treated concomitantly.

6 ADVERSE REACTIONS

The following adverse reactions are included in more detail in the Warnings and Precautions section of the label:

- Cardiac arrhythmias [see Warnings and Precautions (5.1, 5.2)]
- Digoxin Toxicity [see Warnings and Precautions (5.3)]

6.1 Clinical Trials Experience

Because clinical trials are conducted under widely varying conditions, adverse reaction rates observed in the clinical trials of a drug cannot be directly compared to rates in the clinical trials of another drug and may not reflect the rates observed in clinical practice.

In general, the adverse reactions of LANOXIN are dose-dependent and occur at doses higher than those needed to achieve a therapeutic effect. Hence, adverse reactions are less common when LANOXIN is used within the recommended dose range, is maintained within the therapeutic serum concentration range, and when there is careful attention to concurrent medications and conditions.

In the DIG trial (a trial investigating the effect of digoxin on mortality and morbidity in patients with heart failure), the incidence of hospitalization for suspected digoxin toxicity was 2% in patients taking LANOXIN compared to 0.9% in patients taking placebo [see Clinical Studies (14.1)].

The overall incidence of adverse reactions with digoxin has been reported as 5-20%, with 15-20% of adverse events considered serious. Cardiac toxicity accounts for about one-half, gastrointestinal disturbances for about one-fourth, and CNS and other toxicity for about one-fourth of these adverse events.

Gastrointestinal: In addition to nausea and vomiting, the use of digoxin has been associated with abdominal pain, intestinal ischemia, and hemorrhagic necrosis of the intestines.

CNS: Digoxin can cause headache, weakness, dizziness, apathy, confusion, and mental disturbances (such as anxiety, depression, delirium, and hallucination).

Other: Gynecomastia has been occasionally observed following the prolonged use of digoxin. Thrombocytopenia and maculopapular rash and other skin reactions have been rarely observed.

7 DRUG INTERACTIONS

Digoxin has a narrow therapeutic index, increased monitoring of serum digoxin concentrations and for potential signs and symptoms of clinical toxicity is necessary when initiating, adjusting, or discontinuing drugs that may interact with digoxin. Prescribers should consult the prescribing information of any drug which is co-prescribed with digoxin for potential drug interaction information.

7.1 P-Glycoprotein (PGP) Inducers/Inhibitors

Digoxin is a substrate of P-glycoprotein, at the level of intestinal absorption, renal tubular section and biliary-intestinal secretion. Therefore, drugs that induce/inhibit P-glycoprotein have the potential to alter digoxin pharmacokinetics.

7.2 Pharmacokinetic Drug Interactions

Digoxin concentrations increased greater than 50%
 | Digoxin Serum Concentration Increase | Digoxin AUC Increase | Recommendations
Amiodarone | 70% | NA | Measure serum digoxin concentrations before initiating concomitant drugs. Reduce digoxin concentrations by decreasing dose by approximately 30-50% or by modifying the dosing frequency and continue monitoring.
Captopril | 58% | 39% | Measure serum digoxin concentrations before initiating concomitant drugs. Reduce digoxin concentrations by decreasing dose by approximately 30-50% or by modifying the dosing frequency and continue monitoring.
Clarithromycin | NA | 70% | Measure serum digoxin concentrations before initiating concomitant drugs. Reduce digoxin concentrations by decreasing dose by approximately 30-50% or by modifying the dosing frequency and continue monitoring.
Dronedarone | NA | 150% | Measure serum digoxin concentrations before initiating concomitant drugs. Reduce digoxin concentrations by decreasing dose by approximately 30-50% or by modifying the dosing frequency and continue monitoring.
Gentamicin | 129-212% | NA | Measure serum digoxin concentrations before initiating concomitant drugs. Reduce digoxin concentrations by decreasing dose by approximately 30-50% or by modifying the dosing frequency and continue monitoring.
Erythromycin | 100% | NA | Measure serum digoxin concentrations before initiating concomitant drugs. Reduce digoxin concentrations by decreasing dose by approximately 30-50% or by modifying the dosing frequency and continue monitoring.
Itraconazole | 80% | NA | Measure serum digoxin concentrations before initiating concomitant drugs. Reduce digoxin concentrations by decreasing dose by approximately 30-50% or by modifying the dosing frequency and continue monitoring.
Lapatinib | NA | 180% | Measure serum digoxin concentrations before initiating concomitant drugs. Reduce digoxin concentrations by decreasing dose by approximately 30-50% or by modifying the dosing frequency and continue monitoring.
Propafenone | NA | 60-270% | Measure serum digoxin concentrations before initiating concomitant drugs. Reduce digoxin concentrations by decreasing dose by approximately 30-50% or by modifying the dosing frequency and continue monitoring.
Quinidine | 100% | NA | Measure serum digoxin concentrations before initiating concomitant drugs. Reduce digoxin concentrations by decreasing dose by approximately 30-50% or by modifying the dosing frequency and continue monitoring.
Ranolazine | 50% | NA | Measure serum digoxin concentrations before initiating concomitant drugs. Reduce digoxin concentrations by decreasing dose by approximately 30-50% or by modifying the dosing frequency and continue monitoring.
Ritonavir | NA | 86% | Measure serum digoxin concentrations before initiating concomitant drugs. Reduce digoxin concentrations by decreasing dose by approximately 30-50% or by modifying the dosing frequency and continue monitoring.
Telaprevir | 50% | 85% | Measure serum digoxin concentrations before initiating concomitant drugs. Reduce digoxin concentrations by decreasing dose by approximately 30-50% or by modifying the dosing frequency and continue monitoring.
Tetracycline | 100% | NA | Measure serum digoxin concentrations before initiating concomitant drugs. Reduce digoxin concentrations by decreasing dose by approximately 30-50% or by modifying the dosing frequency and continue monitoring.
Verapamil | 50-75% | NA | Measure serum digoxin concentrations before initiating concomitant drugs. Reduce digoxin concentrations by decreasing dose by approximately 30-50% or by modifying the dosing frequency and continue monitoring.
Digoxin concentrations increased less than 50%
Atorvastatin | 22% | 15% | Measure serum digoxin concentrations before initiating concomitant drugs. Reduce digoxin concentrations by decreasing the dose by approximately 15-30% or by modifying the dosing frequency and continue monitoring.
Carvedilol | 16% | 14% | Measure serum digoxin concentrations before initiating concomitant drugs. Reduce digoxin concentrations by decreasing the dose by approximately 15-30% or by modifying the dosing frequency and continue monitoring.
Conivaptan | 33% | 43% | Measure serum digoxin concentrations before initiating concomitant drugs. Reduce digoxin concentrations by decreasing the dose by approximately 15-30% or by modifying the dosing frequency and continue monitoring.
Diltiazem | 20% | NA | Measure serum digoxin concentrations before initiating concomitant drugs. Reduce digoxin concentrations by decreasing the dose by approximately 15-30% or by modifying the dosing frequency and continue monitoring.
Indomethacin | 40% | NA | Measure serum digoxin concentrations before initiating concomitant drugs. Reduce digoxin concentrations by decreasing the dose by approximately 15-30% or by modifying the dosing frequency and continue monitoring.
Mirabegron | 29% | 27% | Measure serum digoxin concentrations before initiating concomitant drugs. Reduce digoxin concentrations by decreasing the dose by approximately 15-30% or by modifying the dosing frequency and continue monitoring.
Nefazodone | 27% | 15% | Measure serum digoxin concentrations before initiating concomitant drugs. Reduce digoxin concentrations by decreasing the dose by approximately 15-30% or by modifying the dosing frequency and continue monitoring.
Nifedipine | 45% | NA | Measure serum digoxin concentrations before initiating concomitant drugs. Reduce digoxin concentrations by decreasing the dose by approximately 15-30% or by modifying the dosing frequency and continue monitoring.
Propantheline | 24% | 24% | Measure serum digoxin concentrations before initiating concomitant drugs. Reduce digoxin concentrations by decreasing the dose by approximately 15-30% or by modifying the dosing frequency and continue monitoring.
Quinine | NA | 33% | Measure serum digoxin concentrations before initiating concomitant drugs. Reduce digoxin concentrations by decreasing the dose by approximately 15-30% or by modifying the dosing frequency and continue monitoring.
Rabeprazole | 29% | 19% | Measure serum digoxin concentrations before initiating concomitant drugs. Reduce digoxin concentrations by decreasing the dose by approximately 15-30% or by modifying the dosing frequency and continue monitoring.
Saquinavir | 27% | 49% | Measure serum digoxin concentrations before initiating concomitant drugs. Reduce digoxin concentrations by decreasing the dose by approximately 15-30% or by modifying the dosing frequency and continue monitoring.
Spironolactone | 25% | NA | Measure serum digoxin concentrations before initiating concomitant drugs. Reduce digoxin concentrations by decreasing the dose by approximately 15-30% or by modifying the dosing frequency and continue monitoring.
Telmisartan | 20-49% | NA | Measure serum digoxin concentrations before initiating concomitant drugs. Reduce digoxin concentrations by decreasing the dose by approximately 15-30% or by modifying the dosing frequency and continue monitoring.
Ticagrelor | 31% | 28% | Measure serum digoxin concentrations before initiating concomitant drugs. Reduce digoxin concentrations by decreasing the dose by approximately 15-30% or by modifying the dosing frequency and continue monitoring.
Tolvaptan | 30% | 20% | Measure serum digoxin concentrations before initiating concomitant drugs. Reduce digoxin concentrations by decreasing the dose by approximately 15-30% or by modifying the dosing frequency and continue monitoring.
Trimethoprim | 22-28% | NA | Measure serum digoxin concentrations before initiating concomitant drugs. Reduce digoxin concentrations by decreasing the dose by approximately 15-30% or by modifying the dosing frequency and continue monitoring.
Digoxin concentrations increased, but magnitude is unclear
Alprazolam, azithromycin, cyclosporine, diclofenac, diphenoxylate, epoprostenol, esomeprazole, ibuprofen, ketoconazole, lansoprazole, metformin, omeprazole |  |  | Measure serum digoxin concentrations before initiating concomitant drugs. Continue monitoring and reduce digoxin dose as necessary.
Digoxin concentrations decreased
Acarbose, activated charcoal, albuterol, antacids, certain cancer chemotherapy or radiation therapy, cholestyramine, colestipol, extenatide, kaolin-pectin, meals high in bran, metoclopramide, miglitol, neomycin, penicillamine, phenytoin, rifampin, St. John’s Wort, sucralfate, sulfasalazine |  |  | Measure serum digoxin concentrations before initiating concomitant drugs. Continue monitoring and increase digoxin dose by approximately 20-40% as necessary.

NA – Not available/reported

7.3 Potentially Significant Pharmacodynamic Drug Interactions

Because of considerable variability of pharmacodynamic interactions, the dosage of digoxin should be individualized when patients receive these medications concurrently.

Drugs that Affect Renal Function | A decline in GFR or tubular secretion, as from ACE inhibitors, angiotensin receptor blockers, nonsteroidal anti-inflammatory drugs [NSAIDS], COX-2 inhibitors may impair the excretion of digoxin.
Antiarrthymics | Dofetilide | Concomitant administration with digoxin was associated with a higher rate of torsades de pointes
 | Sotalol | Proarrhythmic events were more common in patients receiving sotalol and digoxin than on either alone; it is not clear whether this represents an interaction or is related to the presence of CHF, a known risk factor for proarrhythmia, in patients receiving digoxin.
 | Dronedarone | Sudden death was more common in patients receiving digoxin with dronedarone than on either alone; it is not clear whether this represents an interaction or is related to the presence of advanced heart disease, a known risk factor for sudden death in patients receiving digoxin.
Parathyroid Hormone Analog | Teriparatide | Sporadic case reports have suggested that hypercalcemia may predispose patients to digitalis toxicity. Teriparatide transiently increases serum calcium.
Thyroid supplement | Thyroid | Treatment of hypothyroidism in patients taking digoxin may increase the dose requirements of digoxin.
Sympathomimetics | Epinephrine Norepinephrine Dopamine | Can increase the risk of cardiac arrhythmias
Neuromuscular Blocking Agents | Succinylcholine | May cause sudden extrusion of potassium from muscle cells causing arrhythmias in patients taking digoxin.
Supplements | Calcium | If administered rapidly by intravenous route, can produce serious arrhythmias in digitalized patients.
Beta-adrenergic blockers and calcium channel blockers |  | Additive effects on AV node conduction can result in bradycardia and advanced or complete heart block.
Hyperpolarization-activated cyclic nucleotide-gated channel blocker | Ivabradine | Can increase the risk of bradycardia

7.4 Drug/Laboratory Test Interactions

Endogenous substances of unknown composition (digoxin-like immunoreactive substances, [DLIS]) can interfere with standard radioimmunoassays for digoxin. The interference most often causes results to be falsely positive or falsely elevated, but sometimes it causes results to be falsely reduced. Some assays are more subject to these failings than others. Several LC/MS/MS methods are available that may provide less susceptibility to DLIS interference. DLIS are present in up to half of all neonates and in varying percentages of pregnant women, patients with hypertrophic cardiomyopathy, patients with renal or hepatic dysfunction, and other patients who are volume-expanded for any reason. The measured levels of DLIS (as digoxin equivalents) are usually low (0.2-0.4 ng/mL), but sometimes they reach levels that would be considered therapeutic or even toxic.

In some assays, spironolactone, canrenone, and potassium canrenoate may be falsely detected as digoxin, at levels up to 0.5 ng/mL. Some traditional Chinese and Ayurvedic medicine substances like Chan Su, Siberian Ginseng, Asian Ginseng, Ashwagandha or Dashen can cause similar interference.

Spironolactone and DLIS are much more extensively protein-bound than digoxin. As a result, assays of free digoxin levels in protein-free ultrafiltrate (which tend to be about 25% less than total levels, consistent with the usual extent of protein binding) are less affected by spironolactone or DLIS. It should be noted that ultrafiltration does not solve all interference problems with alternative medicines. The use of an LC/MS/MS method may be the better option according to the good results it provides, especially in terms of specificity and limit of quantization.

8 USE IN SPECIFIC POPULATIONS

8.1 Pregnancy

Risk Summary
Experience with digoxin in pregnant women over several decades, based on published retrospective clinical studies and case reports, has not led to the identification of a drug associated risk of major birth defects, miscarriage or adverse maternal and fetal outcomes. Untreated underlying maternal conditions, such as heart failure and atrial fibrillation, during pregnancy pose a risk to mother and fetus (see clinical consideration). Animal reproduction studies have not been conducted with digoxin.
The estimated background risk of major birth defects and miscarriage for the indicated population(s) are unknown. All pregnancies have a background risk of birth defect, loss, or other adverse outcomes. In the U.S. general population, the estimated background risk of major birth defects and miscarriage in clinically recognized pregnancies is 2%-4% and 15%-20%, respectively.

Clinical Considerations
Disease-associated maternal and/or embryo/fetal risk
Pregnant women with heart failure are at increased risk of preterm birth. Clinical classification of heart disease may worsen with pregnancy and lead to maternal or fetal death.
Pregnant women with atrial fibrillation are at increased risk of delivering a low birth weight infant. Atrial fibrillation may worsen with pregnancy and can lead to maternal or fetal death.
Fetal/neonatal adverse reactions
Digoxin has been shown to cross the placenta and is found in amniotic fluid. Monitor neonates for signs and symptoms of digoxin toxicity, including vomitting, cardiac arrhythmias [see Warning and Precautions (5.3)].
Dose adjustments during pregnancy and the postpartum period
LANOXIN requirements may increase during pregnancy and decrease in the postpartum period. Monitor serum digoxin levels during pregnancy and postpartum period [see Dosage and Administration (2.5)].
Labor or delivery
Risk of arrhythmias may increase duing labor and delivery. Monitor patients continously during labor and delivery [see Warnings and Precautions (5.1and 5.2)].

8.2 Lactation

Risk Summary
The digoxin dose received through breastfeeding is upto 4% of the neonatal maintenance dosage, which is unlikely to be clinically relevant. There are no data on the effects of digoxin on the breastfed infant or effects on milk production.
Data
Based on data from two lactation studies in a total of 13 breastfed infants, the digoxin concentrations in breast milk were between 0.4 - 1.0 ng/ml following 0.25 mg once daily dose of digoxin in the lactating mother. Thus, the amount of digoxin ingested daily by the infants is estimated to be between 0.03 to 0.16 μg/kg/day. This translates to relative infant dose of digoxin between 1 to 7% of maternal weight-adjusted dose and about 0.2 to 4% of the neonatal maintenance dose.

8.4 Pediatric Use

The safety and effectiveness of LANOXIN in the control of ventricular rate in children with atrial fibrillation have not been established.

The safety and effectiveness of LANOXIN in the treatment of heart failure in children have not been established in adequate and well-controlled studies. However, in published literature of children with heart failure of various etiologies (e.g., ventricular septal defects, anthracycline toxicity, patent ductus arteriosus), treatment with digoxin has been associated with improvements in hemodynamic parameters and in clinical signs and symptoms.

Newborn infants display considerable variability in their tolerance to digoxin. Premature and immature infants are particularly sensitive to the effects of digoxin, and the dosage of the drug must not only be reduced but must be individualized according to their degree of maturity.

8.5 Geriatric Use

The majority of clinical experience gained with digoxin has been in the elderly population. This experience has not identified differences in response or adverse effects between the elderly and younger patients. However, this drug is known to be substantially excreted by the kidney, and the risk of toxic reactions to this drug may be greater in patients with impaired renal function. Because elderly patients are more likely to have decreased renal function, care should be taken in dose selection, which should be based on renal function, and it may be useful to monitor renal function [see Dosage and Administration (2.1)].

8.6 Renal Impairment

The clearance of digoxin can be primarily correlated with the renal function as indicated by creatinine clearance. Tables 3 and 5 provide the usual daily maintenance dose requirements for digoxin based on creatinine clearance [see Dosage and Administration (2.3)].

Digoxin is primarily excreted by the kidneys; therefore, patients with impaired renal function require smaller than usual maintenance doses of digoxin [see Dosage and Administration (2.3)]. Because of the prolonged elimination half-life, a longer period of time is required to achieve an initial or new steady-state serum concentration in patients with renal impairment than in patients with normal renal function. If appropriate care is not taken to reduce the dose of digoxin, such patients are at high risk for toxicity, and toxic effects will last longer in such patients than in patients with normal renal function.

8.7 Hepatic Impairment

Plasma digoxin concentrations in patients with acute hepatitis generally fall within the range of profiles in a group of healthy subjects.

8.8 Malabsorption

The absorption of digoxin is reduced in some malabsorption conditions such as chronic diarrhea.

10 OVERDOSAGE

10.1 Signs and Symptoms in Adults and Children

The signs and symptoms of toxicity are generally similar to those described in the Adverse Reactions (6.1) but may be more frequent and can be more severe. Signs and symptoms of digoxin toxicity become more frequent with levels above 2 ng/mL. However, in deciding whether a patient’s symptoms are due to digoxin, the clinical state together with serum electrolyte levels and thyroid function are important factors [see Dosage and Administration (2)].

Adults: The most common signs and symptoms of digoxin toxicity are nausea, vomiting, anorexia, and fatigue that occur in 30-70% of patients who are overdosed. Extremely high serum concentrations produce hyperkalemia especially in patients with impaired renal function. Almost every type of cardiac arrhythmia has been associated with digoxin overdose and multiple rhythm disturbances in the same patient are common. Peak cardiac effects occur 3-6 hours following ingestion and may persist for 24 hours or longer. Arrhythmias that are considered more characteristic of digoxin toxicity are new-onset Mobitz type 1 A-V block, accelerated junctional rhythms, non-paroxysmal atrial tachycardia with A-V block, and bi-directional ventricular tachycardia. Cardiac arrest from asystole or ventricular fibrillation is usually fatal.

Digoxin toxicity is related to serum concentration. As digoxin serum levels increase above 1.2 ng/mL, there is a potential for increase in adverse reactions. Furthermore, lower potassium levels increases the risk for adverse reactions. In adults with heart disease, clinical observations suggest that an overdose of digoxin of 10-15 mg results in death of half of patients. A dose above 25 mg ingested by an adult without heart disease appeared to be uniformly fatal if no Digoxin Immune Fab (DIGIBIND®, DIGIFAB®) was administered.

Among the extra-cardiac manifestations, gastrointestinal symptoms (e.g., nausea, vomiting, anorexia) are very common (up to 80% incidence) and precede cardiac manifestations in approximately half of the patients in most literature reports. Neurologic manifestations (e.g., dizziness, various CNS disturbances), fatigue, and malaise are very common. Visual manifestations may also occur with aberration in color vision (predominance of yellow green) the most frequent. Neurological and visual symptoms may persist after other signs of toxicity have resolved. In chronic toxicity, non-specific extra-cardiac symptoms, such as malaise and weakness, may predominate.

Children: In pediatric patients, signs and symptoms of toxicity can occur during or shortly after the dose of digoxin. Frequent non-cardiac effects are similar to those observed in adults although nausea and vomiting are not seen frequently in infants and small pediatric patients. Other reported manifestations of overdose are weight loss in older age groups, failure to thrive in infants, abdominal pain caused by mesenteric artery ischemia, drowsiness, and behavioral disturbances including psychotic episodes. Arrhythmias and combinations of arrhythmias that occur in adult patients can also occur in pediatric patients although sinus tachycardia, supraventricular tachycardia, and rapid atrial fibrillation are seen less frequently in pediatric patients. Pediatric patients are more likely to develop A-V conduction disturbances, or sinus bradycardia. Any arrhythmia in a child treated with digoxin should be considered related to digoxin until otherwise ruled out. In pediatric patients aged 1-3 years without heart disease, clinical observations suggest that an overdose of digoxin of 6-10 mg would result in death of half of the patients. In the same population, a dose above 10 mg resulted in death if no Digoxin Immune Fab were administered.

10.2 Treatment

Chronic Overdose

If there is suspicion of toxicity, discontinue LANOXIN and place the patient on a cardiac monitor. Correct factors such as electrolyte abnormalities, thyroid dysfunction, and concomitant medications [see Dosage and Administration (2.5)]. Correct hypokalemia by administering potassium so that serum potassium is maintained between 4.0 and 5.5 mmol/L. Potassium is usually administered orally, but when correction of the arrhythmia is urgent and serum potassium concentration is low, potassium may be administered by the intravenous route. Monitor electrocardiogram for any evidence of potassium toxicity (e.g., peaking of T waves) and to observe the effect on the arrhythmia. Avoid potassium salts in patients with bradycardia or heart block. Symptomatic arrhythmias may be treated with Digoxin Immune Fab.

Acute Overdose

Patients who have intentionally or accidently ingested massive doses of digoxin should receive activated charcoal orally or by nasogastric tube regardless of the time since ingestion since digoxin recirculates to the intestine by enterohepatic circulation. In addition to cardiac monitoring, temporarily discontinue LANOXIN until the adverse reaction resolves. Correct factors that may be contributing to the adverse reactions [see Warnings and Precautions (5)]. In particular, correct hypokalemia and hypomagnesemia. Digoxin is not effectively removed from the body by dialysis because of its large extravascular volume of distribution. Life threatening arrhythmias (ventricular tachycardia, ventricular fibrillation, high degree A-V block, bradyarrhythma, sinus arrest) or hyperkalemia requires administration of Digoxin Immune Fab. Digoxin Immune Fab has been shown to be 80-90% effective in reversing signs and symptoms of digoxin toxicity. Bradycardia and heart block caused by digoxin are parasympathetically mediated and respond to atropine. A temporary cardiac pacemaker may also be used. Ventricular arrhythmias may respond to lidocaine or phenytoin. When a large amount of digoxin has been ingested, especially in patients with impaired renal function, hyperkalemia may be present due to release of potassium from skeletal muscle. In this case, treatment with Digoxin Immune Fab is indicated; an initial treatment with glucose and insulin may be needed if the hyperkalemia is life-threatening. Once the adverse reaction has resolved, therapy with LANOXIN may be reinstituted following a careful reassessment of dose.

11 DESCRIPTION

LANOXIN (digoxin) is one of the cardiac (or digitalis) glycosides, a closely related group of drugs having in common specific effects on the myocardium. These drugs are found in a number of plants. Digoxin is extracted from the leaves of Digitalis lanata. The term “digitalis” is used to designate the whole group of glycosides. The glycosides are composed of 2 portions: a sugar and a cardenolide (hence “glycosides”).

Digoxin is described chemically as (3β,5β,12β)-3-[(O-2,6-dideoxy-β-D-ribo-hexopyranosyl-(1→4)-O-2,6-dideoxy-β-D-ribo-hexopyranosyl-(1→4)-2,6-dideoxy-β-D-ribo-hexopyranosyl)oxy]-12,14-dihydroxy-card-20(22)-enolide. Its molecular formula is C41H64O14, its molecular weight is 780.95, and its structural formula is:

Digoxin exists as odorless white crystals that melt with decomposition above 230°C. The drug is practically insoluble in water and in ether; slightly soluble in diluted (50%) alcohol and in chloroform; and freely soluble in pyridine.

LANOXIN is supplied as 62.5 mcg (unscored), 125 mcg (scored), and 250 mcg (scored) tablets for oral administration. Each tablet contains the labeled amount of digoxin USP and the following inactive ingredients: corn and potato starches, lactose and magnesium stearate. The 125 mcg tablets contain D&C Yellow No. 10 and FD&C Yellow No. 6, and the 62.5 mcg tablets contain FD&C Yellow No. 6.

12 CLINICAL PHARMACOLOGY

12.1 Mechanism of Action

All of digoxin’s actions are mediated through its effects on Na-K ATPase. This enzyme, the “sodium pump,” is responsible for maintaining the intracellular milieu throughout the body by moving sodium ions out of and potassium ions into cells. By inhibiting Na-K ATPase, digoxin

- causes increased availability of intracellular calcium in the myocardium and conduction system, with consequent increased inotropy, increased automaticity, and reduced conduction velocity
- indirectly causes parasympathetic stimulation of the autonomic nervous system, with consequent effects on the sino-atrial (SA) and atrioventricular (AV) nodes
- reduces catecholamine reuptake at nerve terminals, rendering blood vessels more sensitive to endogenous or exogenous catecholamines
- increases baroreceptor sensitization, with consequent increased carotid sinus nerve activity and enhanced sympathetic withdrawal for any given increment in mean arterial pressure
- increases (at higher concentrations) sympathetic outflow from the central nervous system (CNS) to both cardiac and peripheral sympathetic nerves
- allows (at higher concentrations) progressive efflux of intracellular potassium, with consequent increase in serum potassium levels.

The cardiologic consequences of these direct and indirect effects are an increase in the force and velocity of myocardial systolic contraction (positive inotropic action), a slowing of the heart rate (negative chronotropic effect), decreased conduction velocity through the AV node, and a decrease in the degree of activation of the sympathetic nervous system and renin-angiotensin system (neurohormonal deactivating effect).

12.2 Pharmacodynamics

The times to onset of pharmacologic effect and to peak effect of preparations of LANOXIN are shown in Table 7.

Table 7. Times to Onset of Pharmacologic Effect and to Peak Effect of Preparations of LANOXIN
Product | Time to Onset of Effecta | Time to Peak Effecta
LANOXIN Tablets | 0.5-2 hours | 2-6 hours
LANOXIN Injection/IV | 5-30 minutesb | 1-4 hours

a Documented for ventricular response rate in atrial fibrillation, inotropic effects and electrocardiographic changes.
b Depending upon rate of infusion.

Hemodynamic Effects: Short- and long-term therapy with the drug increases cardiac output and lowers pulmonary artery pressure, pulmonary capillary wedge pressure, and systemic vascular resistance in patients with heart failure. These hemodynamic effects are accompanied by an increase in the left ventricular ejection fraction and a decrease in end-systolic and end-diastolic dimensions.

ECG Changes: The use of therapeutic doses of LANOXIN may cause prolongation of the PR interval and depression of the ST segment on the electrocardiogram. LANOXIN may produce false positive ST-T changes on the electrocardiogram during exercise testing. These electrophysiologic effects are not indicative of toxicity. LANOXIN does not significantly reduce heart rate during exercise.

12.3 Pharmacokinetics

Note: The following data are from studies performed in adults, unless otherwise stated.

Absorption: Following oral administration, peak serum concentrations of digoxin occur at 1 to 3 hours. Absorption of digoxin from LANOXIN Tablets has been demonstrated to be 60-80% complete compared to an identical intravenous dose of digoxin (absolute bioavailability). When LANOXIN Tablets are taken after meals, the rate of absorption is slowed, but the total amount of digoxin absorbed is usually unchanged. When taken with meals high in bran fiber, however, the amount absorbed from an oral dose may be reduced. Comparisons of the systemic availability and equivalent doses for oral preparations of LANOXIN are shown in Dosage and Administration (2.6).

Digoxin is a substrate for P-glycoprotein. As an efflux protein on the apical membrane of enterocytes, P-glycoprotein may limit the absorption of digoxin.

In some patients, orally administered digoxin is converted to inactive reduction products (e.g., dihydrodigoxin) by colonic bacteria in the gut. Data suggest that 1 in 10 patients treated with digoxin tablets, colonic bacteria will degrade 40% or more of the ingested dose. As a result, certain antibiotics may increase the absorption of digoxin in such patients. Although inactivation of these bacteria by antibiotics is rapid, the serum digoxin concentration will rise at a rate consistent with the elimination half-life of digoxin. Serum digoxin concentration relates to the extent of bacterial inactivation, and may be as much as doubled in some cases [see Drug Interactions (7.2)].

Patients with malabsorption syndromes (e.g., short bowel syndrome, celiac sprue, jejunoileal bypass) may have a reduced ability to absorb orally administered digoxin.

Distribution: Following drug administration, a 6-8 hour tissue distribution phase is observed. This is followed by a much more gradual decline in the serum concentration of the drug, which is dependent on the elimination of digoxin from the body. The peak height and slope of the early portion (absorption/distribution phases) of the serum concentration-time curve are dependent upon the route of administration and the absorption characteristics of the formulation. Clinical evidence indicates that the early high serum concentrations do not reflect the concentration of digoxin at its site of action, but that with chronic use, the steady-state post-distribution serum concentrations are in equilibrium with tissue concentrations and correlate with pharmacologic effects. In individual patients, these post-distribution serum concentrations may be useful in evaluating therapeutic and toxic effects [see Dosage and Administration (2.1)].

Digoxin is concentrated in tissues and therefore has a large apparent volume of distribution (approximately 475-500 L). Digoxin crosses both the blood-brain barrier and the placenta. At delivery, the serum digoxin concentration in the newborn is similar to the serum concentration in the mother. Approximately 25% of digoxin in the plasma is bound to protein. Serum digoxin concentrations are not significantly altered by large changes in fat tissue weight, so that its distribution space correlates best with lean (i.e., ideal) body weight, not total body weight.

Metabolism: Only a small percentage (13%) of a dose of digoxin is metabolized in healthy volunteers. The urinary metabolites, which include dihydrodigoxin, digoxigenin bisdigitoxoside, and their glucuronide and sulfate conjugates, are polar in nature and are postulated to be formed via hydrolysis, oxidation, and conjugation. The metabolism of digoxin is not dependent upon the cytochrome P-450 system, and digoxin is not known to induce or inhibit the cytochrome P-450 system.

Excretion: Elimination of digoxin follows first-order kinetics (that is, the quantity of digoxin eliminated at any time is proportional to the total body content). Following intravenous administration to healthy volunteers, 50-70% of a digoxin dose is excreted unchanged in the urine. Renal excretion of digoxin is proportional to creatinine clearance and is largely independent of urine flow. In healthy volunteers with normal renal function, digoxin has a half-life of 1.5-2 days. The half-life in anuric patients is prolonged to 3.5-5 days. Digoxin is not effectively removed from the body by dialysis, exchange transfusion, or during cardiopulmonary bypass because most of the drug is bound to extravascular tissues.

Special Populations: Geriatrics: Because of age-related declines in renal function, elderly patients would be expected to eliminate digoxin more slowly than younger subjects. Elderly patients may also exhibit a lower volume of distribution of digoxin due to age-related loss of lean muscle mass. Thus, the dosage of digoxin should be carefully selected and monitored in elderly patients [see Use in Specific Populations (8.5)].

Gender: In a study of 184 patients, the clearance of digoxin was 12% lower in female than in male patients. This difference is not likely to be clinically important.

Hepatic Impairment: Because only a small percentage (approximately 13%) of a dose of digoxin undergoes metabolism, hepatic impairment would not be expected to significantly alter the pharmacokinetics of digoxin. In a small study, plasma digoxin concentration profiles in patients with acute hepatitis generally fell within the range of profiles in a group of healthy subjects. No dosage adjustments are recommended for patients with hepatic impairment; however, serum digoxin concentrations should be used as appropriate to help guide dosing in these patients.

Renal Impairment: Since the clearance of digoxin correlates with creatinine clearance, patients with renal impairment generally demonstrate prolonged digoxin elimination half-lives and greater exposures to digoxin. Therefore, titrate carefully in these patients based on clinical response, and based on monitoring of serum digoxin concentrations, as appropriate.

Race: The impact of race differences on digoxin pharmacokinetics have not been formally studied. Because digoxin is primarily eliminated as unchanged drug via the kidney and because there are no important differences in creatinine clearance among races, pharmacokinetic differences due to race are not expected.

13 NONCLINICAL TOXICOLOGY

13.1 Carcinogenesis, Mutagenesis, Impairment of Fertility

Digoxin showed no genotoxic potential in in vitro studies (Ames test and mouse lymphoma). No data are available on the carcinogenic potential of digoxin, nor have studies been conducted to assess its potential to affect fertility.

14 CLINICAL STUDIES

14.1 Chronic Heart Failure

Two 12-week, double-blind, placebo-controlled studies enrolled 178 (RADIANCE trial) and 88 (PROVED trial) adult patients with NYHA Class II or III heart failure previously treated with oral digoxin, a diuretic, and an ACE inhibitor (RADIANCE only) and randomized them to placebo or treatment with LANOXIN Tablets. Both trials demonstrated better preservation of exercise capacity in patients randomized to LANOXIN. Continued treatment with LANOXIN reduced the risk of developing worsening heart failure, as evidenced by heart failure-related hospitalizations and emergency care and the need for concomitant heart failure therapy.

DIG Trial of LANOXIN in Patients with Heart Failure

The Digitalis Investigation Group (DIG) main trial was a 37-week, multicenter, randomized, double-blind mortality study comparing digoxin to placebo in 6800 adult patients with heart failure and left ventricular ejection fraction less than or equal to 0.45. At randomization, 67% were NYHA class I or II, 71% had heart failure of ischemic etiology, 44% had been receiving digoxin, and most were receiving a concomitant ACE inhibitor (94%) and diuretics (82%). As in the smaller trials described above, patients who had been receiving open-label digoxin were withdrawn from this treatment before randomization. Randomization to digoxin was again associated with a significant reduction in the incidence of hospitalization, whether scored as number of hospitalizations for heart failure (relative risk 75%), risk of having at least one such hospitalization during the trial (RR 72%), or number of hospitalizations for any cause (RR 94%). On the other hand, randomization to digoxin had no apparent effect on mortality (RR 99%, with confidence limits of 91-107%).

14.2 Chronic Atrial Fibrillation

Digoxin has also been studied as a means of controlling the ventricular response to chronic atrial fibrillation in adults. Digoxin reduced the resting heart rate, but not the heart rate during exercise.

In 3 different randomized, double-blind trials that included a total of 315 adult patients, digoxin was compared to placebo for the conversion of recent-onset atrial fibrillation to sinus rhythm. Conversion was equally likely, and equally rapid, in the digoxin and placebo groups. In a randomized 120-patient trial comparing digoxin, sotalol, and amiodarone, patients randomized to digoxin had the lowest incidence of conversion to sinus rhythm, and the least satisfactory rate control when conversion did not occur.

In at least one study, digoxin was studied as a means of delaying reversion to atrial fibrillation in adult patients with frequent recurrence of this arrhythmia. This was a randomized, double-blind, 43-patient crossover study. Digoxin increased the mean time between symptomatic recurrent episodes by 54%, but had no effect on the frequency of fibrillatory episodes seen during continuous electrocardiographic monitoring.

16 HOW SUPPLIED/STORAGE AND HANDLING

LANOXIN Tablets have "LANOXIN" on one side and are supplied as follows:

Mcg | Scored | Color | Imprint | NDC 59212-xxxx-xx
Mcg | Scored | Color | Imprint | Bottle/100 | Unit dose/100
62.5 | No | Peach | U3A | 240-55 | Not applicable
125 | Yes | Yellow | Y3B | 242-55 | 242-56
250 | Yes | White | X3A | 249-55 | Not applicable

Store at 25°C (77°F); excursions permitted to 15 to 30°C (59 to 86°F) [See USP Controlled Room Temperature] in a dry place and protect from light. Keep out of reach of children.
Dispense in tight, light-resistant container.

17 PATIENT COUNSELING INFORMATION

- Advise patients that many drugs can interact with LANOXIN. Instruct patients to inform their doctor and pharmacist if they are taking any over the counter medications, including herbal medication, or are started on a new prescription.
- Advise patients to contact their doctor or a health care professional if they experience nausea, vomiting, persistent diarrhea, confusion, weakness, or visual disturbances (including blurred vision, green-yellow color disturbances, halo effect) as these could be signs that the dose of LANOXIN may be too high.
- Advise parents or caregivers that the symptoms of having too high LANOXIN doses may be difficult to recognize in infants and pediatric patients. Symptoms such as weight loss, failure to thrive in infants, abdominal pain, and behavioral disturbances may be indications of digoxin toxicity.
- Instruct the patient to monitor and record their heart rate and blood pressure daily.

LANOXIN is a registered trademark of GlaxoSmithKline.

Manufactured for:

Advanz Pharma (US) Corp.
Bannockburn, IL 60015

©2024. All rights reserved.

PRINCIPAL DISPLAY PANEL - 62.5 mcg

NDC 59212-240-55 100 Tablets

LANOXIN®
(digoxin) Tablets, USP

62.5 mcg

ADVANZ PHARMA

Manufactured for:
Advanz Pharma (US) Corp.
Bannockburn, IL 60015
Made in India RX only

PRINCIPAL DISPLAY PANEL - 125 mcg

NDC 59212-242-55 100 Tablets

LANOXIN®
(digoxin) Tablets, USP

125 mcg

ADVANZ PHARMA

Manufactured for:
Advanz Pharma (US) Corp.
Bannockburn, IL 60015
Made in India RX only

NDC 59212-242-56

UNIT DOSE PACK
100 Tablets (10 blister packs of 10 tablets each)

LANOXIN®
(digoxin) Tablets, USP

125 mcg per tablet

This unit dose packaging is intended for institutional inpatient use.
If dispensed for outpatient use, an appropriate safety closure should be provided.

RX only

ADVANZ PHARMA
See prescribing information for dosage information.

PRINCIPAL DISPLAY PANEL - 250 mcg

NDC 59212-249-55 100 Tablets

LANOXIN®
(digoxin) Tablets, USP

250 mcg

ADVANZ PHARMA
Manufactured for:
Advanz Pharma (US) Corp.
Bannockburn, IL 60015
Made in India RX only